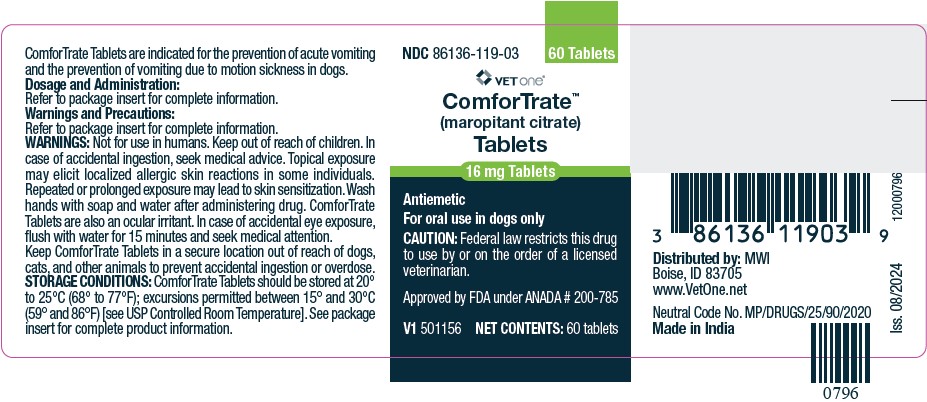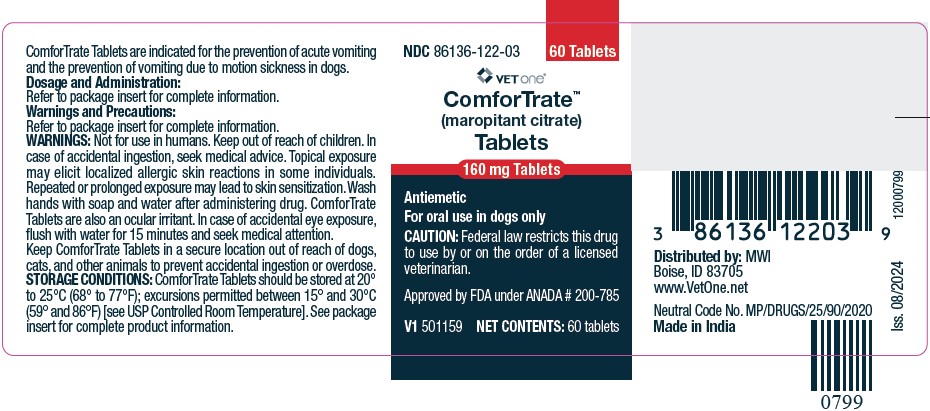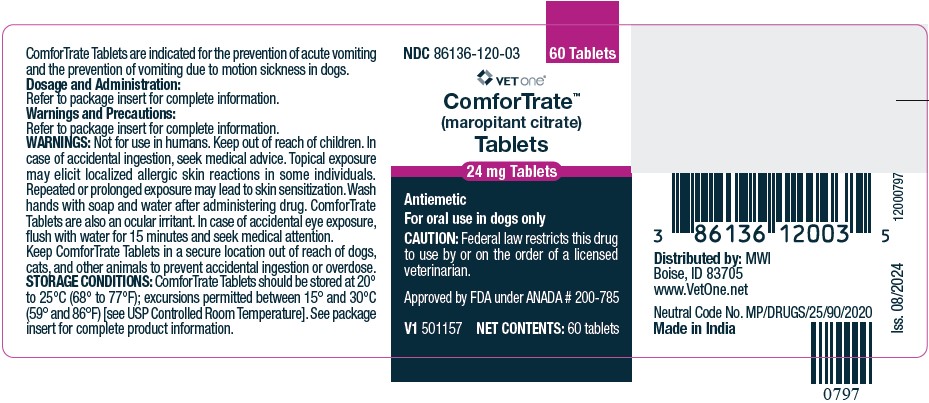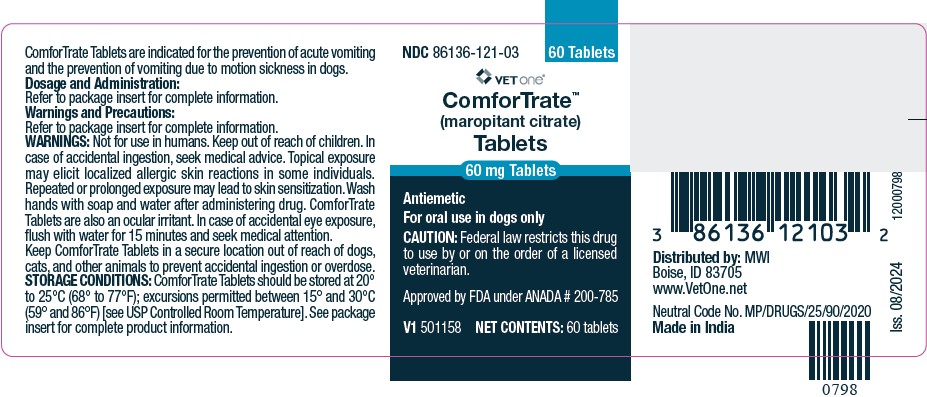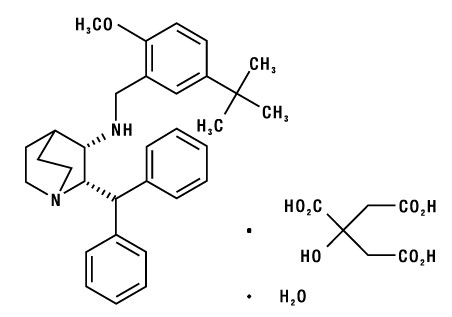 DRUG LABEL: ComforTrate
NDC: 86136-119 | Form: TABLET
Manufacturer: MWI/Vetone
Category: animal | Type: Prescription Animal Drug Label
Date: 20260220

ACTIVE INGREDIENTS: MAROPITANT CITRATE 16 mg/1 1

ComforTrate™
(maropitant citrate)
Tablets
Antiemetic
For oral use in dogs only

CAUTION:

Federal law restricts this drug to use by or on the order of a licensed veterinarian.

DESCRIPTION:

Maropitant is a neurokinin (NK1) receptor antagonist that blocks the pharmacological action of substance P in the central nervous system (CNS). Maropitant is the non-proprietary designation for a substituted quinuclidine. The empirical formula is C32H40N2O C6H8O7 H2O and the molecular weight 678.81. The chemical name is (2S,3S)-2-benzhydryl-N-(5-tert-butyl-2-methoxybenzyl) quinuclidin-3- amine citrate monohydrate. Each light peach to orange mottle colored oval tablet is scored and contains 16, 24, 60 or 160 mg of maropitant as maropitant citrate per tablet.

The chemical structure of maropitant citrate is:

INDICATIONS:

ComforTrateTM Tablets are indicated for the prevention of acute vomiting and the prevention of vomiting due to motion sickness in dogs.

DOSAGE AND ADMINISTRATION:

For Prevention of Acute Vomiting

For Prevention of Acute Vomiting in dogs 2 -7 months of age: Administer ComforTrate Tablets orally at a minimum dose of 2 mg/kg (0.9 mg/lb) body weight once daily for up to 5 consecutive days (see WARNINGSand Animal Safety).

For Prevention of Acute Vomiting in dogs 7 months of age and older: Administer ComforTrate Tablets orally at a minimum dose of 2 mg/kg (0.9 mg/lb) body weight once daily until resolution of acute vomiting.

If vomiting persists despite treatment, the case should be re-evaluated. ComforTrate Tablets is most effective in preventing acute vomiting associated with chemotherapy if administered prior to the chemotherapeutic agent.

For prevention of acute vomiting, dispense whole or half tablets in strength(s) that most closely result in a 2 mg/kg dose:

Dog body weight |  | Number of Tablets
Pounds | Kilograms | 16 mg | 24 mg | 60 mg
8 | 4 | ½
15 | 8 | 1
25 | 12 |  | 1
50 | 24 |  | 2
65 | 30 |  |  | 1
130 | 60 |  |  | 2

Interchangeable use with Maropitant Citrate Injectable Solution for Prevention of Acute Vomiting: In dogs that are actively vomiting, to ensure that the full initial dose is administered, maropitant citrate injectable solution is recommended at a dose of 1 mg/kg once daily. (See package insert for maropitant citrate injectable solution.) Thereafter, for the prevention of acute vomiting, ComforTrate Tablets at a dose of 2 mg/kg once daily may be used interchangeably with maropitant citrate injectable solution for up to 5 days.

For Prevention of Vomiting Due to Motion Sickness in dogs 4 months and older

For Prevention of Vomiting due to motion sickness in dogs 4 months of age and older: Administer ComforTrate Tablets orally at a minimum dose of 8 mg/kg (3.6 mg/lb) body weight once daily for up to 2 consecutive days (see WARNINGSandAnimal Safety).

Administer ComforTrate Tablets a minimum of two hours prior to travel with a small amount of food to mitigate vomiting associated with administration of the dose on an empty stomach; however, refrain from feeding a full meal prior to travel.

Prevention of Vomiting Due to Motion Sickness in Dogs 4 months of age and older:

Dispense whole or half tablets in strengths that most closely result in an 8 mg/kg dose once daily for up to 2 consecutive days:

Dog body weight |  | Number of Tablets
Pounds | Kilograms | 16mg | 24mg | 60mg | 160mg
2 | 1 | 1/2
3 | 1.5 |  | 1/2
4 | 2 | 1
6 | 3 |  | 1
8 | 4 | 2
13 | 6 |  | 2
16 | 7.5 |  |  | 1
22 | 10 |  |  |  | 1/2
33 | 15 |  |  | 2
44 | 20 |  |  |  | 1
66 | 30 |  |  |  | 1 1/2
88 | 40 |  |  |  | 2
132 | 60 |  |  |  | 3

Maropitant citrate injectable solution should not be used interchangeably with ComforTrate Tablets for the prevention of vomiting due to motion sickness (8 mg/kg).

WARNINGS:

Not for use in humans. Keep out of the reach of children. In case of accidental ingestion, seek medical advice. Topical exposure may elicit localized allergic skin reactions in some individuals. Repeated or prolonged exposure may lead to skin sensitization. Wash hands with soap and water after administering drug. ComforTrate Tablets are also an ocular irritant. In case of accidental eye exposure, flush with water for 15 minutes and seek medical attention.

In puppies younger than 11 weeks of age, histological evidence of bone marrow hypocellularity was observed at higher frequency and greater severity in puppies treated with maropitant citrate compared to control puppies. In puppies 16 weeks and older, bone marrow hypocellularity was not observed (see ANIMAL SAFETY).

Keep ComforTrate Tablets in a secure location out of reach of dogs, cats, and other animals to prevent accidental ingestion or overdose.

PRECAUTIONS:

The safe use of ComforTrate Tablets has not been evaluated in dogs used for breeding, or in pregnant or lactating bitches.

The safe use of ComforTrate Tablets has not been evaluated in dogs with gastrointestinal obstruction, or dogs that have ingested toxins.

Use with caution in dogs with hepatic dysfunction because maropitant citrate is metabolized by CYP3A enzymes (see Pharmacokinetics). Use with caution with other medications that are highly protein bound. The concomitant use of ComforTrate Tablets with other protein bound drugs has not been studied in dogs. Commonly used protein bound drugs include NSAIDs, cardiac, anticonvulsant, and behavioral medications. The influence of concomitant drugs that may inhibit the metabolism of ComforTrate Tablets has not been evaluated. Drug compatibility should be monitored in patients requiring adjunctive therapy.

Maropitant citrate causes dose related decreases in appetite and body weight (see ANIMAL SAFETY). To maximize therapeutic potential of ComforTrate Tablets, the underlying cause of vomiting should be identified and addressed in dogs receiving ComforTrate Tablets.

ADVERSE REACTIONS:

Prevention of Acute Vomiting (minimum of 2 mg/kg)

The following adverse reactions were reported during the course of a US field study for the prevention of acute vomiting in dogs treated with maropitant citrate tablets at a minimum of 2 mg/kg orally and/or injectable solution at 1 mg/kg subcutaneously once daily for up to 5 consecutive days:

Frequency of Adverse Reactions by Treatment

Adverse Reaction | Placebo (n=69) |  | maropitant citrate (n=206)
Adverse Reaction | # dogs | % occurrence | # dogs | % occurrence
Death during study | 4 | 5.8 | 10 | 4.9
Euthanized during study | 0 | 0 | 2 | 1
Diarrhea | 6 | 8.7 | 8 | 3.9
Hematochezia/bloody stool | 5 | 7.2 | 4 | 1.9
Anorexia | 2 | 2.9 | 3 | 1.5
Otitis/Otorrhea | 0 | 0 | 3 | 1.5
Endotoxic Shock | 1 | 1.4 | 2 | 1
Hematuria | 0 | 0 | 2 | 1
Excoriation | 0 | 0 | 2 | 1

Other clinical signs were reported but were <0.5% of dogs.

Prevention of Vomiting Due to Motion Sickness (minimum of 8 mg/kg)

The following adverse reactions were reported during US studies for the prevention of vomiting due to motion sickness in dogs treated with maropitant citrate tablets at a minimum of 8 mg/kg orally one time. Dogs may have experienced more than one of the observed adverse reactions.

Frequency of Adverse Reactions by Treatment

Adverse Reaction | Placebo (n=195) |  | maropitant citrate (n=208)
Adverse Reaction | # dogs | % occurrence | # dogs | % occurrence
Hypersalivation | 19 | 9.7 | 26 | 12.5
Vomiting* | 0 | 0 | 11 | 5.3
Muscle Tremors | 1 | 0.5 | 2 | 1
Sedation/Depression | 3 | 1.5 | 2 | 1
Retching | 3 | 1.5 | 1 | 0.5
Flatulence | 0 | 0 | 1 | 0.5

*Not associated with motion sickness.

The following adverse reactions were reported during a European field study for the prevention of vomiting due to motion sickness in dogs treated with maropitant citrate tablets at a minimum of 8 mg/kg orally once daily for 2 consecutive days. Dogs may have experienced more than one of the observed adverse reactions.

Frequency of Adverse Reactions by Treatment

Adverse Reaction | Placebo (n=106) |  | maropitant citrate (n=107)
Adverse Reaction | # dogs | % occurrence | # dogs | % occurrence
Vomiting | 4 | 4 | 10 | 9
Drowsiness/Lethargy/Apathy | 1 | 1 | 8 | 8
Hypersalivation | 2 | 2 | 5 | 5
Anxiety | 0 | 0 | 2 | 2
Trembling/Tremors | 0 | 0 | 2 | 2
Inappetence | 0 | 0 | 2 | 2
Mucus in stool | 0 | 0 | 1 | 1

The following Adverse Reactions were reported during the conduct of a US clinical field trial where maropitant citrate tablets were administered once daily for 28 consecutive days to 32 dogs: lethargy, vomiting, inappetence, corneal edema, and enlarged lymph nodes.

Post-Approval Experience (Revised May 2019)

The following adverse events are based on post-approval adverse drug experience reporting. Not all adverse events are reported to FDA CVM. It is not always possible to reliably estimate the adverse event frequency or establish a causal relationship to product exposure using these data.

The following adverse events reported for dogs are listed in decreasing order of frequency:

anorexia, depression/lethargy, hypersalivation, vomiting, diarrhea, trembling, ataxia, allergic reactions, weight loss, convulsion, hyperactivity, and panting.

Cases of ineffectiveness have been reported.

Cases of death (including euthanasia) have been reported.

Contact Information

To report suspected adverse events, for technical assistance or to obtain a copy of the Safety Data Sheet (SDS), contact Felix Pharmaceuticals Private Limited at 1-833-571-1525. For additional information about adverse drug experience reporting for animal drugs, contact FDA at 1-888-FDA-VETS or http://www.fda.gov/reportanimalae

CLINICAL PHARMACOLOGY:

Pharmacokinetics

Mean (±SD) Plasma Pharmacokinetic Parameters for Maropitant in Beagle Dogs after single dose and repeat oral doses of Maropitant:

PK Parameter | 2 mg/kg Single Dose | 2 mg/kg repeat Doses^1 | 8 mg/kg Single Dose | 8 mg/kg repeat Doses^1
Tmax^2 (hr) | 2.0 (1.5 – 3.0) | 1.5 (1.0 – 3.0) | 1.5 (1.0 – 3.0) | 2.5 (1.5 – 7.0)
Cmax (ng/mL) | 154 (111) | 304 (165) | 588 (416) | 1409 (516)
AUC(0-24) (ng*hr/mL) | 1440 (982) | 3890 (3030) | 6730 (5030) | 26600 (9200)
T1/2^2 (hr) | NC | 7.69 (6.21 - 17.8) | NC | 25.4 (6.06 - 30.0)
Accumulation Ratio (Rac)^3 | NA | 2.46 (1.68, 3.61) | NA | 4.81 (3.28, 7.05)

^1Following once daily doses of maropitant for 14 days.

^2Median (Range)

^3Ratio=Multiple Dose AUC(0-24) /Single Dose AUC(0-24) , Least square means (95% Confidence Interval)

NA= Not Applicable

NC= Not Calculated

Following oral administration, median time to reach Cmax was within 2.5 hr. The absolute bioavailability of maropitant was low (24%) following oral administration of 2 mg/kg maropitant. After an oral dose, prandial status does not significantly affect the extent of oral bioavailability. Greater than dose-proportional drug exposure can be expected with an increase in dose (1-16 mg/kg PO). However as doses increase (20-50 mg/kg PO), the dose proportionality is re-established. Based upon in vitro enzyme kinetics, involvement of a high capacity enzyme (CYP3A12) may contribute to this return to dose linearity. Due to dose dependent pharmacokinetics, the maropitant concentrations reached steady state approximately after 4 and 8 days following 2 and 8 mg/kg, respectively. The observed drug accumulation ratios were 2.46 and 4.81, after oral administration of 2 and 8 mg/kg, respectively. The exposure of 10 week old puppies to maropitant was lower than that observed in adult dogs, particularly after repeat doses of 1 or 2 mg/kg. Systemic clearance of maropitant following IV administration was 970, 995, and 533 mL/hr/kg at doses of 1, 2 and 8 mg/kg, respectively.

Urinary recovery of maropitant and its major metabolite was minimal (<1% each). The hepatic metabolism of maropitant involves two cytochrome P-450 isoenzymes: CYP2D15 and CYP3A12. In in vitro enzyme kinetics data suggest that the non-linear kinetics may be partially associated with saturation of the low capacity enzyme (CYP2D15). Plasma protein binding of maropitant was high (99.5%).

Pharmacodynamics

Vomiting is a complex process coordinated centrally by the emetic center which consists of several brainstem nuclei (area postrema, nucleus tractus solitarius, dorsal motor nucleus of the vagus) that receive and integrate sensory stimuli from central and peripheral sources and chemical stimuli from the circulation and the cerebro-spinal fluid. Maropitant is a neurokinin 1 (NK1) receptor antagonist which acts by inhibiting the binding of substance P, a neuropeptide of the tachykinin family. Substance P is found in significant concentrations in the nuclei comprising the emetic center and is considered the key neurotransmitter involved in emesis.^1 By inhibiting the binding of substance P within the emetic center, maropitant provides broad-spectrum effectiveness against neural (central) and humoral (peripheral) causes of vomiting.

In vivo model studies in dogs have shown that maropitant has antiemetic effectiveness against both central and peripheral emetogens including apomorphine, and syrup of ipecac.

^1Diemunsch P, Grelot L. Potential of substance P antagonists as antiemetics. [Review] [60 refs]. Drugs. 2000;60:533-46.

EFFECTIVENESS:

Prevention of Acute Vomiting

In laboratory model studies, maropitant citrate tablets dosed at a minimum of 2 mg/kg BW reduced the number of emetic events associated with established neural (central) and humoral (peripheral) stimuli. Following administration of apomorphine (central emetic stimuli), vomiting was observed in 33% (4 of 12) of Beagle dogs treated with maropitant citrate tablets and 100% (12 of 12) of Beagle dogs treated with placebo tablets. Following administration of syrup of ipecac (peripheral emetic stimuli) vomiting was observed in 33% (4 of 12) of Beagle dogs treated with maropitant citrate tablets and in 83% (10 of 12) of Beagle dogs treated with placebo tablets.

In a study of 275 canine patients presented to veterinary hospitals with a history of acute vomiting, dogs were initially administered maropitant citrate injectable solution or placebo on Day 0. Following the initial dose, dogs allocated to the maropitant citrate group were treated with either maropitant citrate tablets at a minimum of 2 mg/kg orally or injectable solution at 1 mg/kg subcutaneously once daily at the discretion of the clinician. Dogs allocated to the placebo group were treated using either an injectable placebo solution or placebo tablets once daily at the discretion of the clinician. Of the 199 dogs included in the analysis for effectiveness, 27 of 54 dogs (50%) in the placebo group displayed vomiting at some time during the study and 31 of 145 dogs (21.4%) in the treated group displayed vomiting during the study period.

Percent Of Vomiting For Each Study Day, Based Upon Treatment And Route Of Administration.

Days | Treatment | Route | # dogs | # vomited | % vomited
Day 0 | Placebo (54) | SC | 54 | 15 | 28%
Day 0 | maropitant citrate (145) | SC | 145 (143*) | 14 | 10%
Day 1 | Placebo (45) | PO | 22 | 3 | 14%
Day 1 | Placebo (45) | SC | 23 | 16 | 70%
Day 1 | maropitant citrate (108) | PO | 67 | 2 | 3%
Day 1 | maropitant citrate (108) | SC | 41 | 16 | 39%
Day 2 | Placebo (16) | PO | 7 | 2 | 29%
Day 2 | Placebo (16) | SC | 9 | 6 | 67%
Day 2 | maropitant citrate (37) | PO | 24 | 0 | 0%
Day 2 | maropitant citrate (37) | SC | 13 | 8 | 62%
Day 3 | Placebo (6) | PO | 2 | 0 | 0%
Day 3 | Placebo (6) | SC | 4 | 1 | 25%
Day 3 | maropitant citrate (21) | PO | 14 | 0 | 0%
Day 3 | maropitant citrate (21) | SC | 7 | 5 | 71%
Day 4 | Placebo (2) | PO | 1 | 0 | 0%
Day 4 | Placebo (2) | SC | 1 | 1 | 100%
Day 4 | maropitant citrate (7) | PO | 5 | 0 | 0%
Day 4 | maropitant citrate (7) | SC | 2 | 1 | 50%
Day 5 | maropitant citrate (1) | SC | 1 | 0 | 0%

*2 dogs administered maropitant citrate were not observed on Day 0. Their vomiting status was unknown. 143 was used in the denominator for % vomited.

In US field studies in veterinary patients, maropitant citrate tablets and injectable solution were well tolerated in dogs presenting with various conditions including parvovirus, gastroenteritis, and renal disease. There were no notable differences in mean laboratory values between maropitant citrate-treated and placebo- treated patients.

Maropitant citrate tablets were used safely in dogs receiving other frequently used veterinary products such as fluid and electrolyte replacement solutions, antimicrobial agents, vaccines, antacids, and antiparasitic agents.

Prevention of Vomiting due to Motion Sickness

In a study of canine veterinary patients taken on a one-hour car journey and treated with either maropitant citrate tablets at a minimum dose of 8 mg/kg BW or placebo tablets 2 hours prior to the journey, 67 of 122 (55%) of dogs vomited during the journey when treated with placebo while 8 of 122 (7%) vomited during the journey after treatment with maropitant citrate tablets. The probability that a dog in this study, prone to motion sickness would NOT vomit during a journey if treated with maropitant citrate tablets was 93%, while the probability was 48% if treated with placebo.

ANIMAL SAFETY:

Laboratory and field studies have demonstrated that maropitant citrate tablets are well tolerated in dogs after oral administration.

Target Animal Safety Study for Acute Vomiting

Fifty six Beagle dogs (28 males and 28 females) approximately 16 weeks of age were administered maropitant citrate tablets orally once daily for 15 days at 0, 2, 6, and 10 mg/kg. There were 8 dogs (4 males and 4 females) in the 2 mg/kg group and 16 dogs (8 males and 8 females) in all other groups. Maropitant citrate tablets caused decreases in food consumption and body weight that were not dose-dependent and did not persist after cessation of treatment.

Beagle dogs approximately 8 weeks of age were administered maropitant citrate tablets orally once daily for 15 days at 0, 2, 6, and 10 mg/kg using a protocol similar to the previous study. A dose dependent increase in severity of bone marrow hypoplasia was observed histologically. Interpretation of these study results is complicated by the health status of study animals. Dogs used in the study were weaned early, minimally acclimated to the test facility, many of the dogs in the study tested positive for coccidia and some tested positive for canine parvovirus.

Beagle dogs approximately 10 weeks of age were administered either placebo tablets for 2 days, maropitant citrate tablets at 8 mg/kg for 2 days, placebo (saline) subcutaneously (SC) for 5 days, maropitant citrate injectable solution at 1 mg/kg SC for 5 days, or maropitant citrate tablets at 2 mg/kg for 5 days (8 dogs in each dose group). Mild pain associated with injection was noted in more dogs and lasted longer in dogs that received maropitant injections compared to saline. Males administered maropitant citrate at 8 mg/kg orally for 2 days had a decrease in food consumption. Body weight and food consumption were variable throughout the 4 week acclimation period. Two dogs that received 8 mg/kg maropitant orally for 2 days were below the reference range for reticulocyte counts. Decreases in reticulocyte counts were also seen in 4 (of 8) placebo treated dogs (SC saline for 5 days). Hypocellular femoral bone marrow described as "minimal" was seen in 1 male that received 1 mg/kg maropitant SC for 5 days; reticulocyte counts were not available for this dog.

Twenty four Beagle dogs (12 males and 12 females) 7 months of age were administered maropitant at doses of 0, 1, 5, and 20 mg/kg orally once daily for 93 consecutive days. Maropitant produced sporadic clinical signs (salivation, emesis), body weight loss, and lower serum albumin levels at 20 mg/kg/day. Maropitant increased P-R interval, P wave duration, and QRS amplitude in the 20 mg/kg /day dose group. One female in the 20 mg/kg/day group had increased cellularity of the bone marrow. This female was noted to have lower mean red cell parameters (red blood cell count, hemoglobin, hematocrit) and higher platelet counts and reticulocytes.

Target Animal Safety Study for Motion Sickness

Forty Beagle dogs (20 males and 20 females) between 16 – 18 weeks of age were administered maropitant citrate tablets orally once daily for 6 days at 0, 8 and 24 mg/kg. There were 16 dogs (8 males and 8 females) in the 0 and 24 mg/kg groups and 8 dogs (4 males and 4 females) in the 8 mg/kg group. At 24 mg/kg, maropitant citrate tablets caused decreases in food consumption, with decreases in body weight, liver and testis weight; and an increase in RBC count indicating hemoconcentration, but the effects on feed consumption, body weight, and RBCs did not persist in the post-treatment recovery period (beyond Day 5).

Beagle dogs approximately 8 weeks of age were administered maropitant citrate tablets orally once daily for 6 days at 0, 8, and 24 mg/kg using a protocol similar to the previous study. One dog in the 24 mg/kg/day group died of unknown causes on study day 2 and a dose dependent increase in occurrence and severity of bone marrow hypoplasia and lymphoid depletion was observed histologically. Interpretation of these study results is complicated by the health status of study animals. Dogs used in the study were weaned early, minimally acclimated to the test facility, and many of the dogs in the study tested positive for coccidia. Additionally, some dogs in the study tested positive for canine parvovirus, however, clinical parvoviral disease was not definitively diagnosed.

Tolerance Studies

Twenty four Beagle dogs (14 males and 10 females) between 11 and 25 weeks of age were administered maropitant citrate tablets in 2 phases with 8 dogs per group. In the first phase the dogs were administered 0, 20 or 30 mg/kg orally once daily for 7 days and in the second phase 0, 40, or 50 mg/kg once daily for 7 days. Maropitant citrate tablets administered at 20 and 30 mg/kg caused occasional vomiting. Maropitant citrate tablets administered at 40 mg/kg and 50 mg/kg caused clinically relevant signs of weight loss, vomiting, soft stools, weakness, lethargy, salivation and hypokalemia. Additionally, leukopenia characterized by a neutropenia and a trend toward decreasing plasma phosphorus values was seen. Decreased heart rate and prolonged corrected QT intervals were seen in all treatment groups in a dose dependent manner.

Twenty-four Beagle dogs (12 males and 12 females) approximately 28 weeks of age were administered maropitant (mesylate salt) orally once daily for 90 days at 0, 1, 5, and 20 mg/kg. End of study body weights in the 20 mg/kg group were 8-15% lower than baseline body weights.

STORAGE CONDITIONS:

Store at 20° to 25°C (68° to 77°F); excursions permitted between 15° and 30°C (59° and 86°F) [see USP Controlled Room Temperature].

HOW SUPPLIED:

ComforTrate Tablets are light peach to orange mottle colored, scored with a break line, and contain 16, 24, 60 or 160 mg of maropitant as maropitant citrate per tablet. Each tablet is marked with "F" and “12” on either side of score line on the concave side of the tablet and “16/24/60/160” on the convex side of the tablet. Each tablet size is packaged in a bottle containing 60 tablets.

NDC Number | Tablet Strength | Package Description
86136-119-03 | 16 mg | 60 in Bottle pack
86136-120-03 | 24 mg | 60 in Bottle pack
86136-121-03 | 60 mg | 60 in Bottle pack
86136-122-03 | 160 mg | 60 in Bottle pack

SPL UNCLASSIFIED SECTION

Approved by FDA under ANADA # 200-785

Distributed by: MWI

Boise, ID 83705

www.VetOne.net

Made in India

Neutral Code No. MP/DRUGS/25/90/2020

Iss. 01/2026

PACKAGE LABEL.PRINCIPAL DISPLAY PANEL

16 mg Bottle Label:

NDC 86136-119-03 60 Tablets

ComforTrateTM

(maropitant citrate)

Tablets

16 mg Tablets
Antiemetic
For oral use in dogs only
CAUTION: Federal law restricts this drug to use by or on the order of a licensed veterinarian.
Approved by FDA under ANADA # 200-785

NET CONTENTS: 60 tablets

PACKAGE LABEL.PRINCIPAL DISPLAY PANEL

24 mg Bottle Label:

NDC 86136-120-03 60 Tablets

ComforTrateTM

(maropitant citrate)

Tablets
24 mg Tablets
Antiemetic
For oral use in dogs only
CAUTION: Federal law restricts this drug to use by or on the order of a licensed veterinarian.
Approved by FDA under ANADA # 200-785

NET CONTENTS: 60 tablets

PACKAGE LABEL.PRINCIPAL DISPLAY PANEL

60 mg Bottle Label:

NDC 86136-121-03 60 Tablets

ComforTrateTM

(maropitant citrate)

Tablets
60 mg Tablets
Antiemetic
For oral use in dogs only
CAUTION: Federal law restricts this drug to use by or on the order of a licensed veterinarian.
Approved by FDA under ANADA # 200-785

NET CONTENTS: 60 tablets

PACKAGE LABEL.PRINCIPAL DISPLAY PANEL

160 mg Bottle Label:

NDC 86136-122-03 60 Tablets

ComforTrateTM

(maropitant citrate)

Tablets
160 mg Tablets
Antiemetic
For oral use in dogs only
CAUTION: Federal law restricts this drug to use by or on the order of a licensed veterinarian.
Approved by FDA under ANADA # 200-785

NET CONTENTS: 60 tablets